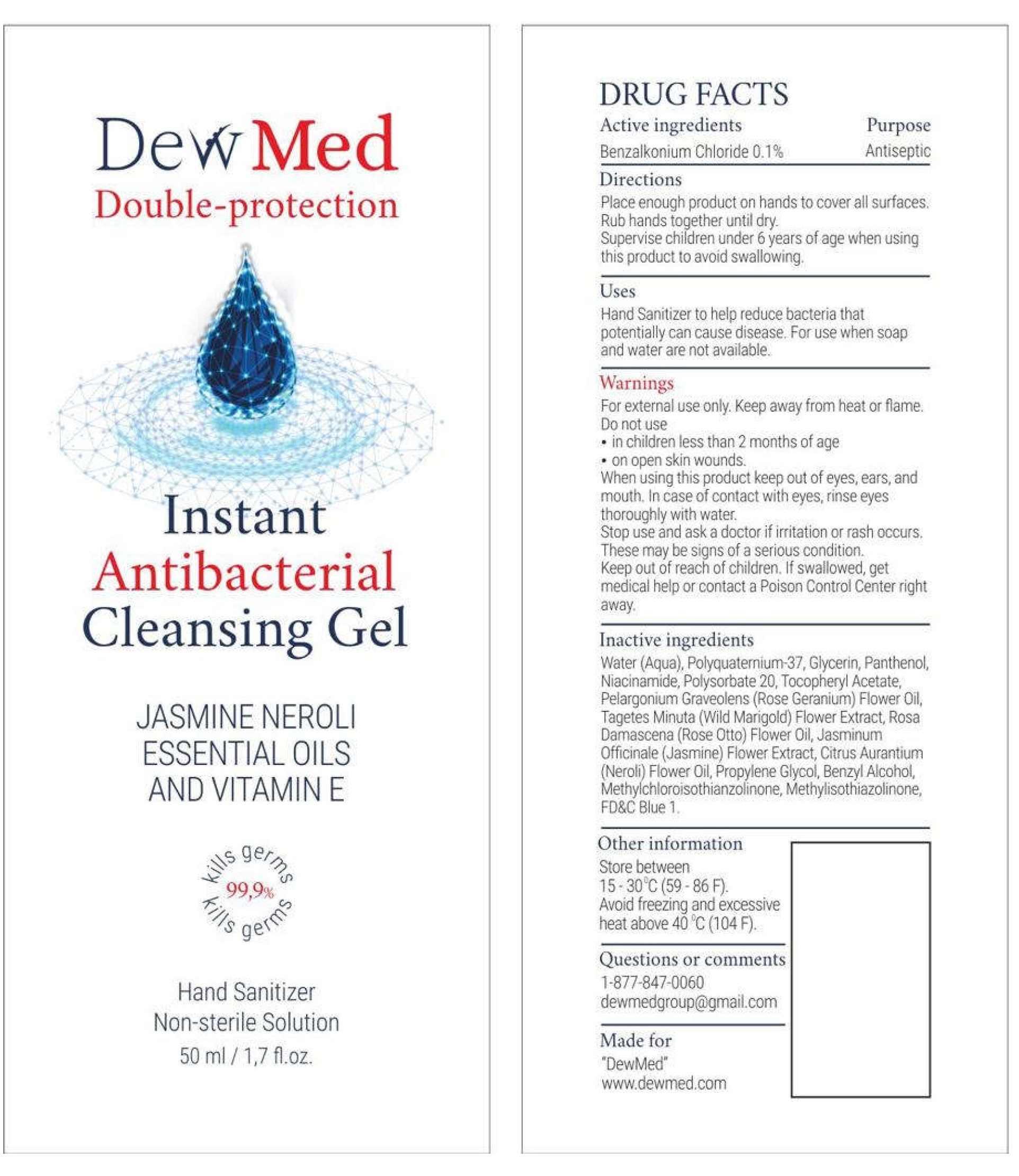 DRUG LABEL: DewMed Instant Antibacterial Cleansing Hand Sanitizer
NDC: 80065-001 | Form: GEL
Manufacturer: DewMed LLC
Category: otc | Type: HUMAN OTC DRUG LABEL
Date: 20200917

ACTIVE INGREDIENTS: BENZALKONIUM CHLORIDE 1 mg/1 mL
INACTIVE INGREDIENTS: WATER; POLYQUATERNIUM-37 (10000 MPA.S); GLYCERIN; PANTHENOL; NIACINAMIDE; POLYSORBATE 20; .ALPHA.-TOCOPHEROL ACETATE; PELARGONIUM GRAVEOLENS FLOWER OIL; TAGETES MINUTA FLOWER OIL; ROSA X DAMASCENA FLOWER OIL; JASMINUM OFFICINALE FLOWER; CITRUS AURANTIUM FLOWER OIL; PROPYLENE GLYCOL; BENZYL ALCOHOL; METHYLCHLOROISOTHIAZOLINONE; METHYLISOTHIAZOLINONE; FD&C BLUE NO. 1

DewMed Instant Antibacterial Cleansing Gel Hand Sanitizer

Active ingredients

Benzalkonium Chloride 0.1%

Purpose

Antiseptic

Directions

Place enough product on hands to cover all surfaces. Rub hands together until dry.
Supervise children under 6 years of age when using this product to avoid swallowing.

Uses

Hand Sanitizer to help reduce bacteria that potentially can cause disease. For use when soap and water are not available.

Warnings

For external use only. Keep away from heat or flame.

Do not use

- in children less than 2 months of age
- on open skin wounds.

When using this product

keep out of eyes, ears, and mouth. In case of contact with eyes, rinse eyes thoroughly with water.

Stop use and ask a doctor

if irritation or rash occurs. These may be signs of a serious condition.

Keep out of reach of children.

If swallowed, get medical help or contact a Poison Control Center right away.

Inactive ingredients

Water (Aqua), Polyquaternium-37, Glycerin, Panthenol, Niacinamide, Polysorbate 20, Tocopheryl Acetate, Pelargonium Graveolens (Rose Geranium) Flower Oil, Tagetes Minuta (Wild Marigold) Flower Extract, Rosa Damascena (Rose Otto) Flower Oil, Jasminum Officinale (Jasmine) Flower Extract, Citrus Aurantinum (Neroli) Flower Oil, Propylene Glycol, Benzyl Alcohol, Methlchloroisothiazolinone, Methylisothiazolinone, FD&C Blue 1.

Other information

Store between 15-30°C (59-86F).
Avoid freezing and excessive heat above 40°C (104F).

Questions or comments

1-877-847-0060 dewmedgroup@gmail.com